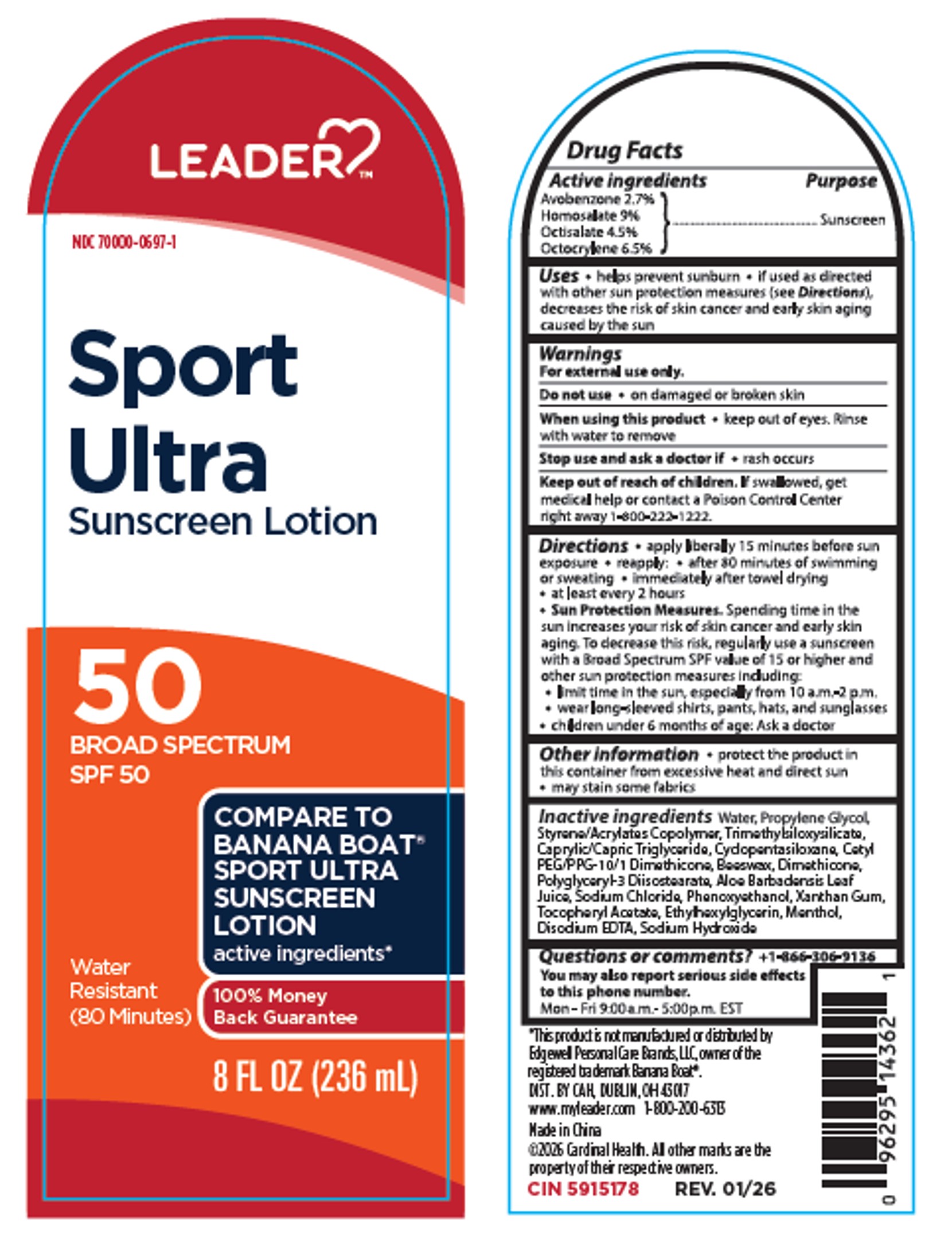 DRUG LABEL: Leader Sport Ultra Sunscreen SPF 50
NDC: 70000-0697 | Form: LOTION
Manufacturer: CARDINAL HEALTH 110, LLC. DBA LEADER
Category: otc | Type: HUMAN OTC DRUG LABEL
Date: 20251208

ACTIVE INGREDIENTS: OCTISALATE 4.5 g/100 mL; OCTOCRYLENE 6.5 g/100 mL; AVOBENZONE 2.7 g/100 mL; HOMOSALATE 9 g/100 mL
INACTIVE INGREDIENTS: MENTHOL; SODIUM HYDROXIDE; TRIMETHYLSILOXYSILICATE (M/Q 0.8-1.0); CAPRYLIC/CAPRIC TRIGLYCERIDE; CYCLOPENTASILOXANE; PROPYLENE GLYCOL; CETYL PEG/PPG-10/1 DIMETHICONE (HLB 2); PHENOXYETHANOL; BEESWAX; DIMETHICONE; POLYGLYCERYL-3 DIISOSTEARATE; ALOE BARBADENSIS LEAF JUICE; SODIUM CHLORIDE; XANTHAN GUM; .ALPHA.-TOCOPHEROL ACETATE; WATER; EDETATE DISODIUM; ETHYLHEXYLGLYCERIN

Active Ingredients

Avobenzone 2.7%, Homosalate 9%, Octisalate 4.5%, Octocrylene 6.5%

Purpose

Sunscreen

Uses

• helps prevent sunburn • If used as directed with other sun protectiion measures (see Directions), decreases the risk of skin cancer and early skin aging caused by the sun.

Warnings

For external use only.

Flammable:

• keep away from fire or flame

• wait 10 minutes after application before approaching a source of heat or flame, or before smoking

Do not use

• on damaged or broken skin.

When using this product

• Keep out of eyes. Rinse with water to remove

Stop use and ask a doctor if

• rash occurs.

Keep out of reach of children.

If product is swallowed, get medical help or contact a Poison Control Center right away 1-800-222-1222.

Directions

• Apply liberally 15 minutes before sun exposure

• reapply:

• after 80 minues of swimming or sweating

• immediately after towel drying

• at least every 2 hours

• Sun Protection Measures.

Spending time in the sun increases your risk of skin cancer and early skin aging. To decrease this risk, regularly use a sunscreen with a broad spectrum SPF of 15 or higher and other sun protection measures including:

• limit time in the sun, especially from 10:00 a.m.-2:00 p.m.

• wear long-sleeve shirts, pants, hats, and sunglasses

• children under 6 months of age: Ask a doctor.

Inactive ingredients

WATER, PROPYLENE GLYCOL, STYRENE/ACRYLATES COPOLYMER, TRIMETHYLSILOXYSILICATE, CAPRYLIC/CAPRIC TRIGLYCERIDE, CYCLOPENTASILOXANE, CETYL PEG/PPG-10/1 DIMETHICONE, BEESWAX, DIMETHICONE, POLYGLYCERYL-3 DIISOSTEARATE, ALOE BARBADENSIS LEAF JUICE, SODIUM CHLORIDE, PHENOXYETHANOL, XANTHAN GUM, TOCOPHERYL ACETATE, ETHYLHEXYLGLYCERIN, MENTHOL, DISODIUM EDTA, SODIUM HYDROXIDE

Other Information

• protect the product in this container from excessive heat and direct sun

• may stain some fabrics

Questions or comments?

+1-866-306-9136

You may also report serious side effects to this phone number.

Mon - Fri 9:00 a.m. - 5:00 p.m. EST